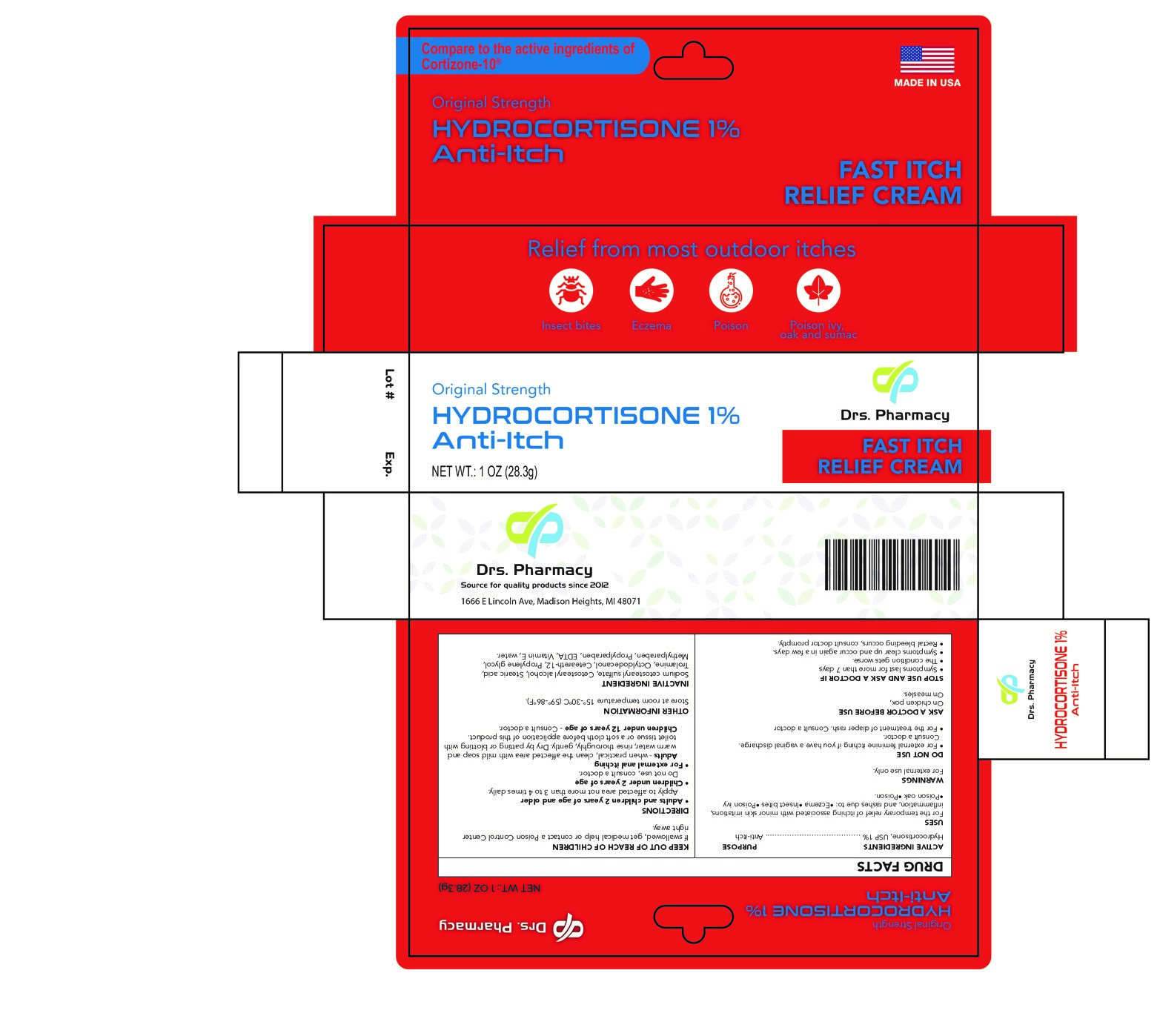 DRUG LABEL: Hydrocortisone
NDC: 80489-001 | Form: CREAM
Manufacturer: OL PHARMA TECH,LLC
Category: otc | Type: HUMAN OTC DRUG LABEL
Date: 20260122

ACTIVE INGREDIENTS: HYDROCORTISONE 10 mg/1 g
INACTIVE INGREDIENTS: CETEARETH-12; PROPYLENE GLYCOL; METHYLPARABEN; EDETATE DISODIUM; TROLAMINE; SODIUM CETOSTEARYL SULFATE; PROPYLPARABEN; WATER; CETOSTEARYL ALCOHOL; MINERAL OIL; .ALPHA.-TOCOPHEROL; STEARIC ACID

ACTIVE INGREDIENT

Hydrocortisone, USP 1%

PURPOSE

Anti-itch

USES

for the temporary relief of itching associated with minor skin irritations, inflammation, and rashes due to:

•eczema

•insect bites

•poison ivy

•poison oak

•poison ...

WARNINGS

For external use only

DO NOT USE

for external feminine itching if you have a vaginal discharge. Consult a doctor.
for the treatment of diaper rash. Consult a doctor.

WHEN USING THIS PRODUCT

•avoid contact with the eyes

•do not begin the use of any other hydrocortisone product unless directed by a doctor

•for external anal itching:

do not use more than directed unless directed by a doctor

do not put this product into the rectum by using fingers or any mechanical device or applicator

STOP USE AND ASK YOUR DOCTOR IF

•symptoms last for more than 7 days

•the condition gets worse

•symptoms clear up and occur again in a few days

•rectal bleeding occurs, consult doctor promptly

Keep out of reach of children. If swallowed, get medical help or contact a Poison Control Center right away.

DIRECTIONS

- Adults and children 2 years of age and older: apply to affected area not more than 3 to 4 times daily
- Children under 2 years of age: do not use, consult a doctor
- For external anal itching
- Adults: when practical, clean the affected area with mild soap and warm water, rinse thoroughly, gently dry by patting or blotting with toilet tissue or a soft cloth before application of this product

OTHER INFORMATION

- Store at room temperature 59°-86°F (15°-30°C).
- Protect from freezing.
- Before using any medication, read all label directions. Keep carton, it contains important information.

INACTIVE INGREDIENTS

cetostearyl alcohol, sodium cetostearyl sulfate, stearic acid, trolamine, mineral oil , propylene glycol, water, methyl paraben, propyl paraben, EDTA, vitamin E

PACKAGE LABEL

original strenghth

fast itch relief cream